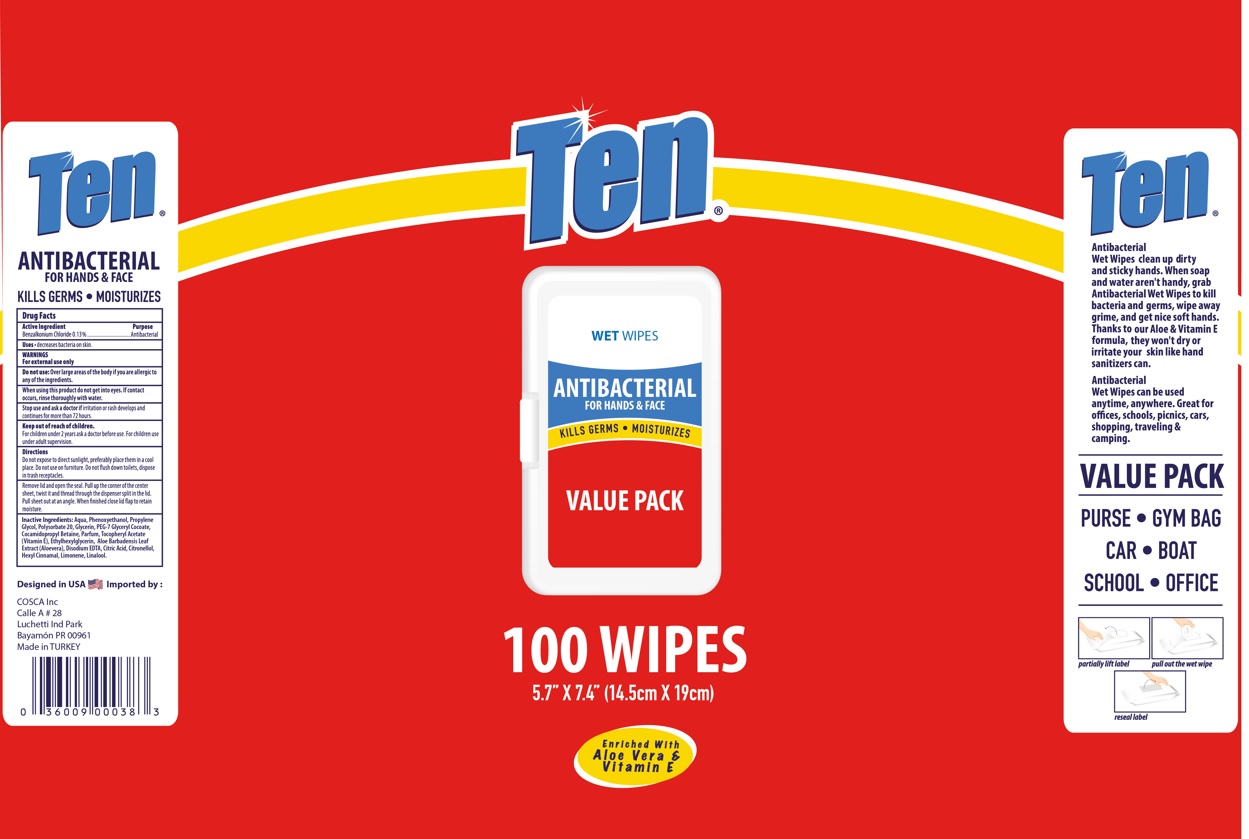 DRUG LABEL: Wet wipes
NDC: 78564-006 | Form: CLOTH
Manufacturer: TAHA KIMYA KOZMETIK VE TUKETIM URUNLERI SANAYI PAZARLAMA ANONIM SIRKETI
Category: otc | Type: HUMAN OTC DRUG LABEL
Date: 20230601

ACTIVE INGREDIENTS: BENZALKONIUM CHLORIDE 0.13 mg/100 1
INACTIVE INGREDIENTS: EDETATE DISODIUM ANHYDROUS; .ALPHA.-TOCOPHEROL ACETATE; .BETA.-CITRONELLOL, (R)-; GLYCERIN; PEG-7 GLYCERYL COCOATE; ETHYLHEXYLGLYCERIN; CITRIC ACID MONOHYDRATE; POLYSORBATE 20; COCAMIDOPROPYL BETAINE; ALOE VERA LEAF; .ALPHA.-HEXYLCINNAMALDEHYDE; LIMONENE, (+)-; WATER; PROPYLENE GLYCOL; LINALOOL, (+/-)-; PHENOXYETHANOL

JinTu, Wipes, Benzalkonium chloride

Active ingredient

Benzalkonium Chloride 0.13% w/w. Purpose: Antibacteria

Purpose

Antibacterial

WHEN USING

decreases bacteria on skin

Do not use

- in children less than 2 months of age
- on open skin

Stop use and ask a doctor if irritation or rash occurs. These may be signs of a serious condition.

Keep out of reach of children. If swallowed, get medical help or contact a Poison Control Center right away.

Directions

Do not expose to direct sunlight, preferably place them in a cool place. Do not use on furniture. Do not flush down toilets. dispose in trash receptacles.

Remove lid and open the seal. Pull up the conrer of the center sheet, twist it and thread through the dispenser split in the lid. Pull sheet out at an angle. When finished close lid flap to retain moisture.

Directions

Peel back flap on front to pull out a wipe.

Unfold and wipe hands thoroughly.

Reseal and let hands dry.

No need to rinse.

Warnings

For external use only. Flammable. Keep away from heat or flame

- Do not replace wipes used for medical procedures.
- These wipes are meant for general cleansing.

Other information

Store between 15-30℃ (59-86℉)

Inactive ingredients

water, phenoxyethanol, propylene glycol, polysorbate 20, peg-7 glyceryl cocoate, cocamidopropyl betaine, parfum, tocopheryl acetate, ethylhexylglycerin, aloe barbadensis leaf extract, disodium edta, citric acid, citronellol, hexyl cinnamal, limonene, linalool.